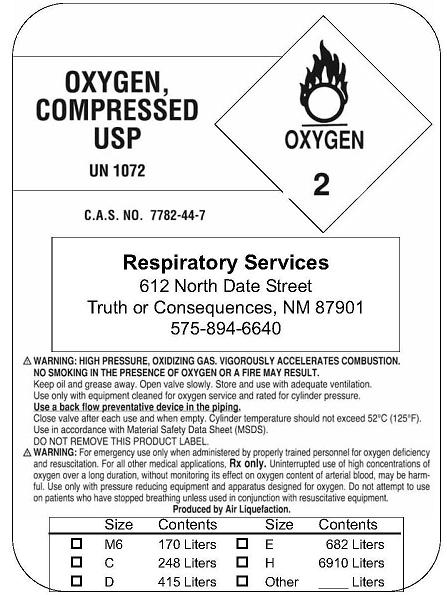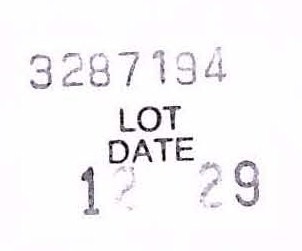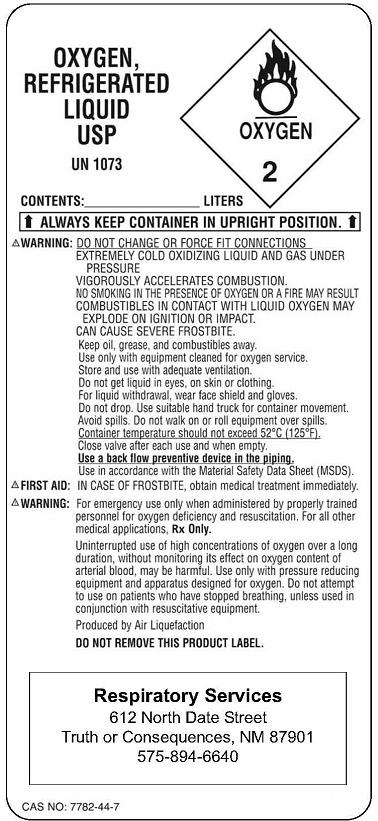 DRUG LABEL: Oxygen
NDC: 62187-0001 | Form: GAS
Manufacturer: Deborah Stubblefield dba Respiratory Services
Category: prescription | Type: HUMAN PRESCRIPTION DRUG LABEL
Date: 20091218

ACTIVE INGREDIENTS: Oxygen 99 L/100 L

Oxygen